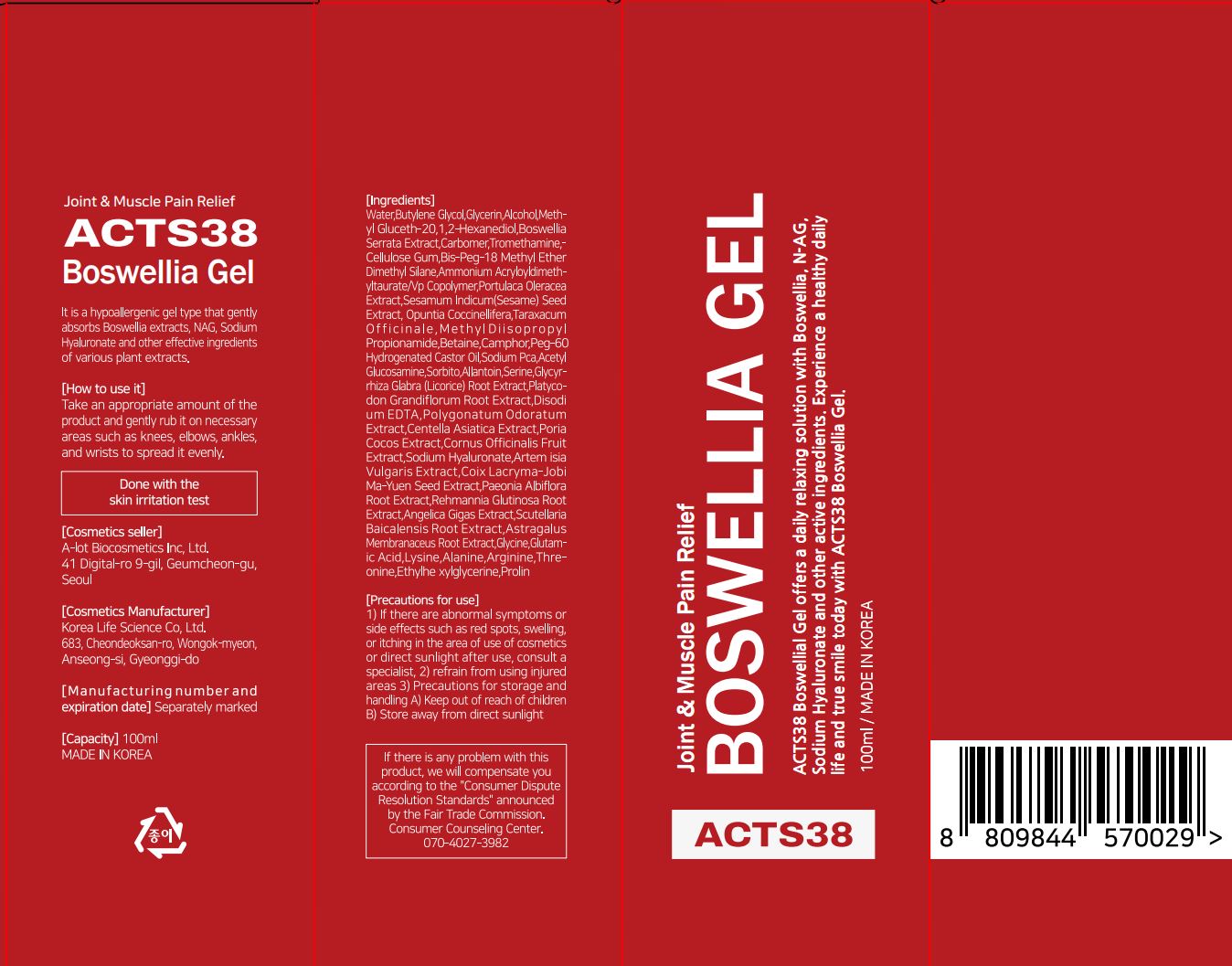 DRUG LABEL: ACTS38 BoswelliaGel (100ml)
NDC: 82967-0002 | Form: GEL
Manufacturer: A-Lot Biologics Inc
Category: otc | Type: HUMAN OTC DRUG LABEL
Date: 20221022

ACTIVE INGREDIENTS: N-ACETYLGLUCOSAMINE 0.1 g/100 mL; HYALURONATE SODIUM 0.01 g/100 mL; INDIAN FRANKINCENSE 1.2 g/100 mL; CENTELLA ASIATICA 0.01 g/100 mL
INACTIVE INGREDIENTS: WATER

Drug Facts

ACTIVE INGREDIENT

- Boswellia Serrata Extract
- Acetyl Glucosamine
- Centella Asiatica Extract
- Sodium Hyaluronate

PURPOSE

Simply massage the ACT38 over painful areas for beneficial effects including:
- Pain relief for Arthritic Pain, Neck and Shoulder Pain, Back Pain and more
- Decrease in joint swelling
- Improved blood supply to inflamed joints
- Increasing joint suppleness
- Powerful anti-inflammatory effects
- Relieves stiff and sore muscles

KEEP OUT OF REACH OF THE CHILDREN

INDICATIONS AND USAGE

Take an appropriate amount of the product and gently rub it on necessary areas such as knees,
elbows, ankles, and wrists to spread it evenly.

WARNINGS

1) If there are abnormal symptoms or side effects such as red spots, swelling, or itching in the
area of use of cosmetics or direct sunlight after use, consult a specialist
2) refrain from using injured areas
3) Precautions for storage and handling
A) Keep out of reach of children
B) Store away from direct sunlight

DOSAGE AND ADMINISTRATION

for external use only

INACTIVE INGREDIENT

Water
Butylene Glycol
Glycerin
Alcohol
Methyl Gluceth-20
1,2-Hexanediol
Boswellia Serrata Extract(12,000ppm)
Carbomer
Tromethamine
Cellulose Gum
Bis-Peg-18 Methyl Ether Dimethyl Silane
Ammonium Acryloyldimethyltaurate/Vp
Copolymer
Portulaca Oleracea Extract
Opuntia Coccinellifera
Taraxacum Officinale
Sesamum Indicum(Sesame) Seed Extract
Methyl Diisopropyl Propionamide
Betaine
Camphor
Peg-60 Hydrogenated Castor Oil
Glycyrrhiza Glabra (Licorice) Root Extract
Platycodon Grandiflorum Root Extract
Poria Cocos Extract
Sodium Pca
Acetyl Glucosamine
Coix Lacryma-Jobi Ma-Yuen Seed Extract
Paeonia Albiflora Root Extract
Angelica Gigas Extract
Polygonatum Odoratum Extract
Artemisia Vulgaris Extract
Cornus Officinalis Fruit Extract
Rehmannia Glutinosa Root Extract
Scutellaria Baicalensis Root Extract
Astragalus Membranaceus Root Extract
Sorbitol
Allantoin
Serine
Disodium Edta
Centella Asiatica Extract
Sodium Hyaluronate
Glycine
Glutamic Acid
Lysine
Alanine
Arginine
Threonine
Ethylhexylglycerine
Prolin